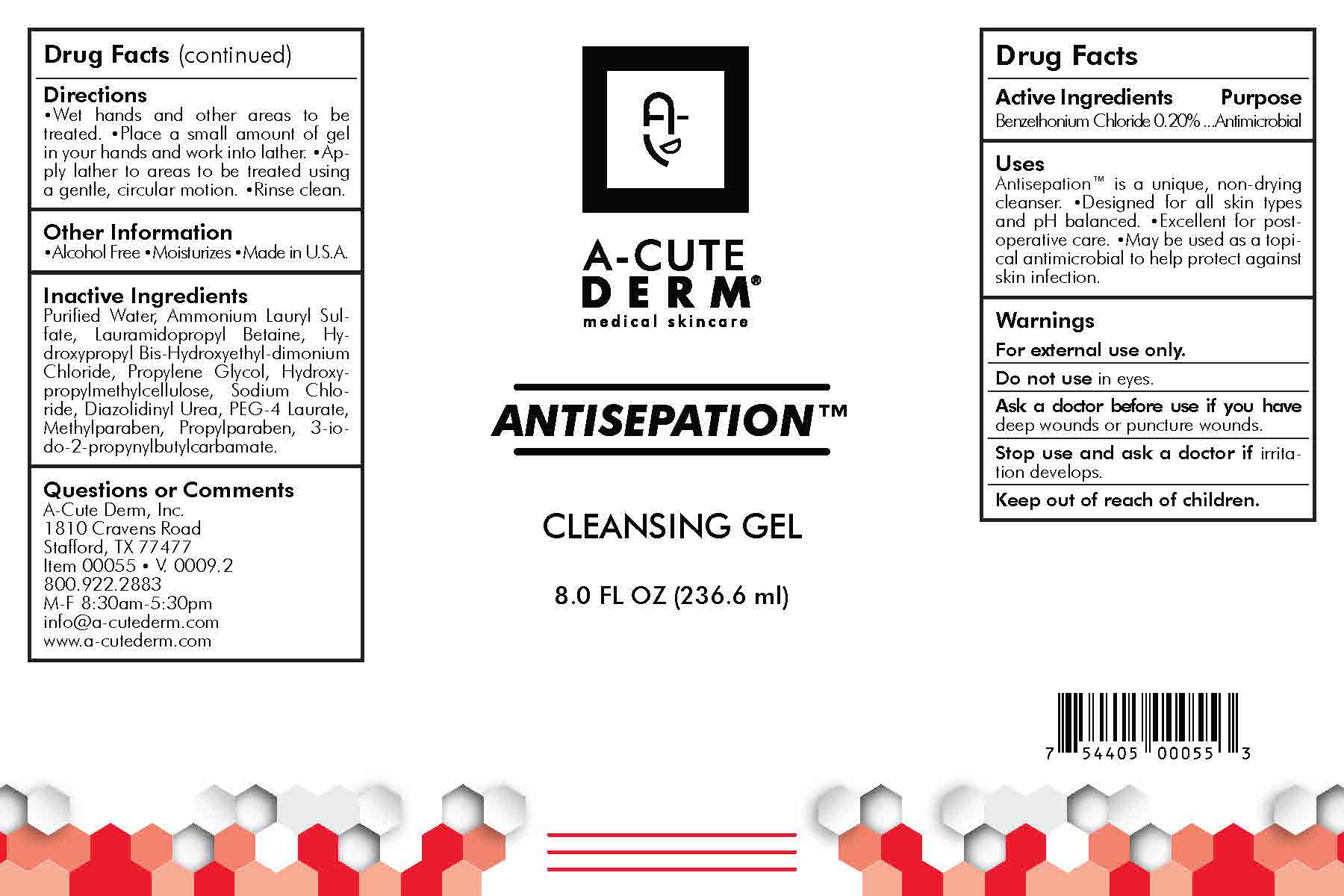 DRUG LABEL: Antisepation
NDC: 61619-717 | Form: LOTION
Manufacturer: A-Cute Derm, Incorporated
Category: otc | Type: HUMAN OTC DRUG LABEL
Date: 20211223

ACTIVE INGREDIENTS: BENZETHONIUM CHLORIDE 2 mg/1 mL
INACTIVE INGREDIENTS: AMMONIUM LAURYL SULFATE; HYDROXYPROPYL BIS-HYDROXYETHYLDIMONIUM CHLORIDE; HYPROMELLOSES; SODIUM CHLORIDE; DIAZOLIDINYL UREA; PEG-4 LAURATE; METHYLPARABEN; IODOPROPYNYL BUTYLCARBAMATE; LAURAMIDOPROPYL BETAINE; PROPYLPARABEN; PROPYLENE GLYCOL; WATER

DRUG FACTS

Antimicrobial

Active Ingredients

Benzethonium Chloride (0.2%)

Purpose

Antimicrobial

Uses

Antisepation™ is a unique, non-drying cleanser. •Designed for all skin types and pH balanced. •Excellent for postoperative care. •May be used as a topical antimicrobial to help protect against skin infection.

Warnings

For external use only.
Do not use in eyes.
Ask a doctor before use if you have deep wounds or puncture wounds.
Stop use and ask a doctor if irritation develops.

Directions

•Wet hands and other areas to be treated.

•Place a small amount of gel in your

hands and work into lather. •Apply lather

to areas to be treated using a gentle, circular

motion. •Rinse clean.

Other Information

•Alcohol Free •Moisturizes •Made in USA

Inactive ingredients

Purified Water, Ammonium Lauryl Sulfate,

Lauramidopropyl Betaine, Hydroxypropyl

Bis-Hydroxyethyl-dimonium Chloride,

Propylene Glycol, Hydroxypropylmethylcellulose,

Sodium Chloride, Diazolidinyl

Urea, PEG-4 Laurate, Methylparaben,

Propylparaben, 3-iodo-2-propynylbutylcarbamate.

Questions or Comments

A-Cute Derm, Inc.

1810 Cravens Road

Stafford, TX 77477

800.922.2883

M-F 8:30am-5:30pm

info@a-cutederm.com

www.a-cutederm.com

Principal Display Panel

Antisepation cleansing gel